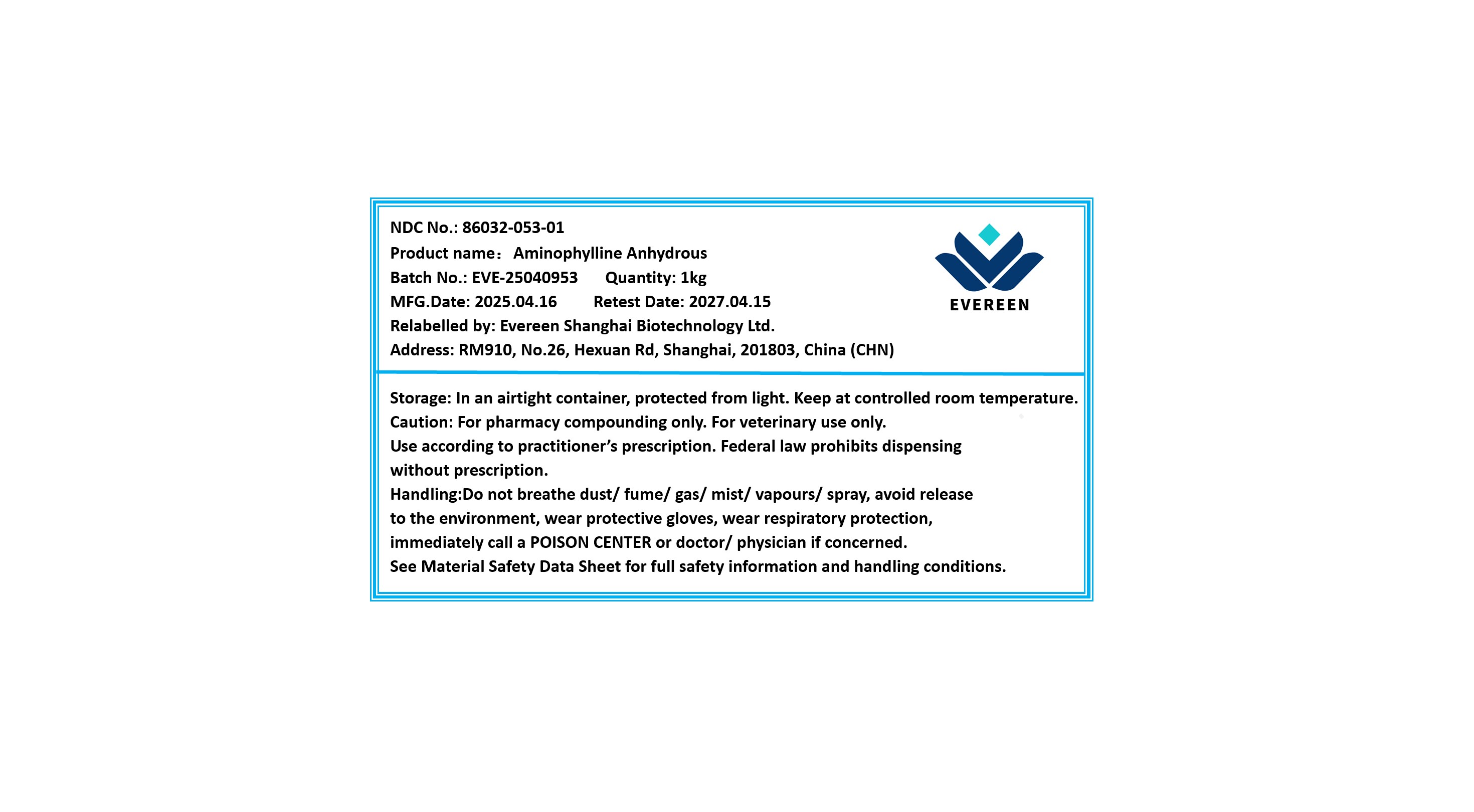 DRUG LABEL: Aminophylline Anhydrous
NDC: 86032-053 | Form: POWDER
Manufacturer: Evereen Shanghai Biotechnology Ltd.
Category: other | Type: BULK INGREDIENT - ANIMAL DRUG
Date: 20250613

ACTIVE INGREDIENTS: ADENOSINE PHOSPHATE 1 kg/1 kg

Aminophylline Anhydrous